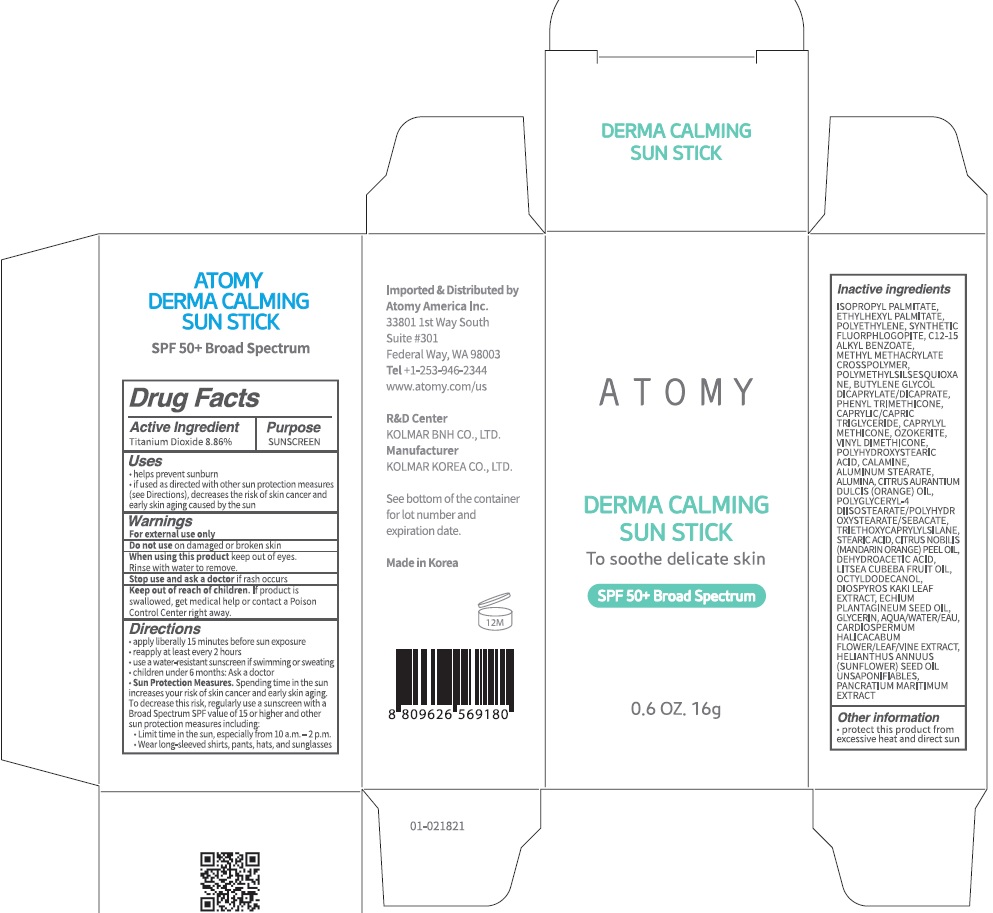 DRUG LABEL: ATOMY DERMA CALMING SUN
NDC: 52257-1400 | Form: STICK
Manufacturer: ATOMY CO., LTD.
Category: otc | Type: HUMAN OTC DRUG LABEL
Date: 20240130

ACTIVE INGREDIENTS: Titanium Dioxide 1.41 g/16 g
INACTIVE INGREDIENTS: ISOPROPYL PALMITATE; ETHYLHEXYL PALMITATE

ACTIVE INGREDIENT

Titanium Dioxide 8.86%

INACTIVE INGREDIENTS

ISOPROPYL PALMITATE, ETHYLHEXYL PALMITATE, POLYETHYLENE, SYNTHETIC FLUORPHLOGOPITE, C12-15 ALKYL BENZOATE, METHYL METHACRYLATE CROSSPOLYMER, POLYMETHYLSILSESQUIOXANE, BUTYLENE GLYCOL DICAPRYLATE/DICAPRATE, PHENYL TRIMETHICONE, CAPRYLIC/CAPRIC TRIGLYCERIDE, CAPRYLYL METHICONE, OZOKERITE, VINYL DIMETHICONE, POLYHYDROXYSTEARIC ACID, CALAMINE, ALUMINUM STEARATE, ALUMINA, CITRUS AURANTIUM DULCIS (ORANGE) OIL, POLYGLYCERYL-4 DIISOSTEARATE/POLYHYDR OXYSTEARATE/SEBACATE, TRIETHOXYCAPRYLYLSILANE, STEARIC ACID, CITRUS NOBILIS (MANDARIN ORANGE) PEEL OIL, DEHYDROACETIC ACID, LITSEA CUBEBA FRUIT OIL, OCTYLDODECANOL, DIOSPYROS KAKI LEAF EXTRACT, ECHIUM PLANTAGINEUM SEED OIL, GLYCERIN, AQUA/WATER/EAU, CARDIOSPERMUM HALICACABUM FLOWER/LEAF/VINE EXTRACT, HELIANTHUS ANNUUS (SUNFLOWER) SEED OIL UNSAPONIFIABLES, PANCRATIUM MARITIMUM EXTRACT

PURPOSE

Sunscreen

WARNINGS

For external use only
Do not use on damaged or broken skin
When using this product keep out of eyes. Rinse with water to remove.
Stop use and ask a doctor if rash occurs
Keep out of reach of children. If product is swallowed, get medical help or contact a Poison Control Center right away.

KEEP OUT OF REACH OF CHILDREN

If product is swallowed, get medical help or contact a Poison Control Center right away.

Uses

• Helps prevent sunburn

• If used as directed with other sun protection measures
(see Directions), decreases the risk of skin cancer and early skin aging caused by the sun

Directions

• Apply liberally 15 minutes before sun exposure
• Reapply at least every 2 hours
• Use a water-resistant sunscreen if swimming or sweating
• Children under 6 months: Ask a doctor
• Sun Protection Measures. Spending time in the sun increases your risk of skin cancer and early skin aging.
To decrease this risk, regularly use a sunscreen with a Broad Spectrum SPF value of 15 or higher and other sun protection measures including:
• Limit time in the sun, especially from 10 a.m. ‒ 2 p.m.
• Wear long-sleeved shirts, pants, hats, and sunglasses

Other information

Protect this product from excessive heat and direct sun